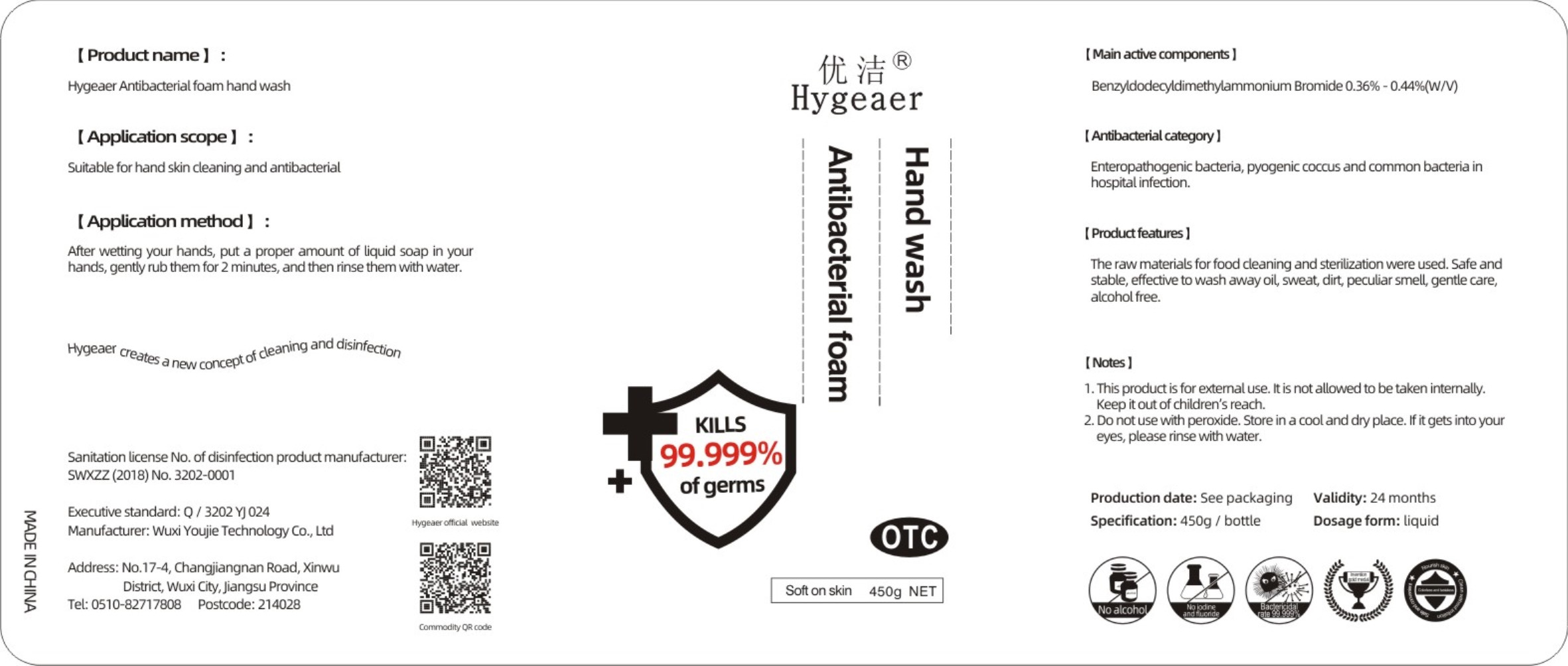 DRUG LABEL: Antibacterial foam hand wash
NDC: 54796-001 | Form: LIQUID
Manufacturer: Wuxi Youjie Technology Co. LTD
Category: otc | Type: HUMAN OTC DRUG LABEL
Date: 20200428

ACTIVE INGREDIENTS: BENZALKONIUM BROMIDE 1.8 g/450 g
INACTIVE INGREDIENTS: WATER

DOSAGE AND ADMINISTRATION

Store in a cool and dry place.

INACTIVE INGREDIENT

water

INDICATIONS AND USAGE

After wetting your hands, put a proper amount of liquid soap in your hands, gently rub them for 2 minutes, and then rinse them with water.

ACTIVE INGREDIENT

BENZALKONIUM BROMIDE

keep out of reach of children

PURPOSE

Disinfection
Sterilization

WARNINGS

1. This productis for extemaluse. Itis not allowed to be taken intemally.Keep it out of children's reach.
2. Do not use with peroxide. Store in a cool and dry place. If it gets into your eyes, please rinse with water.